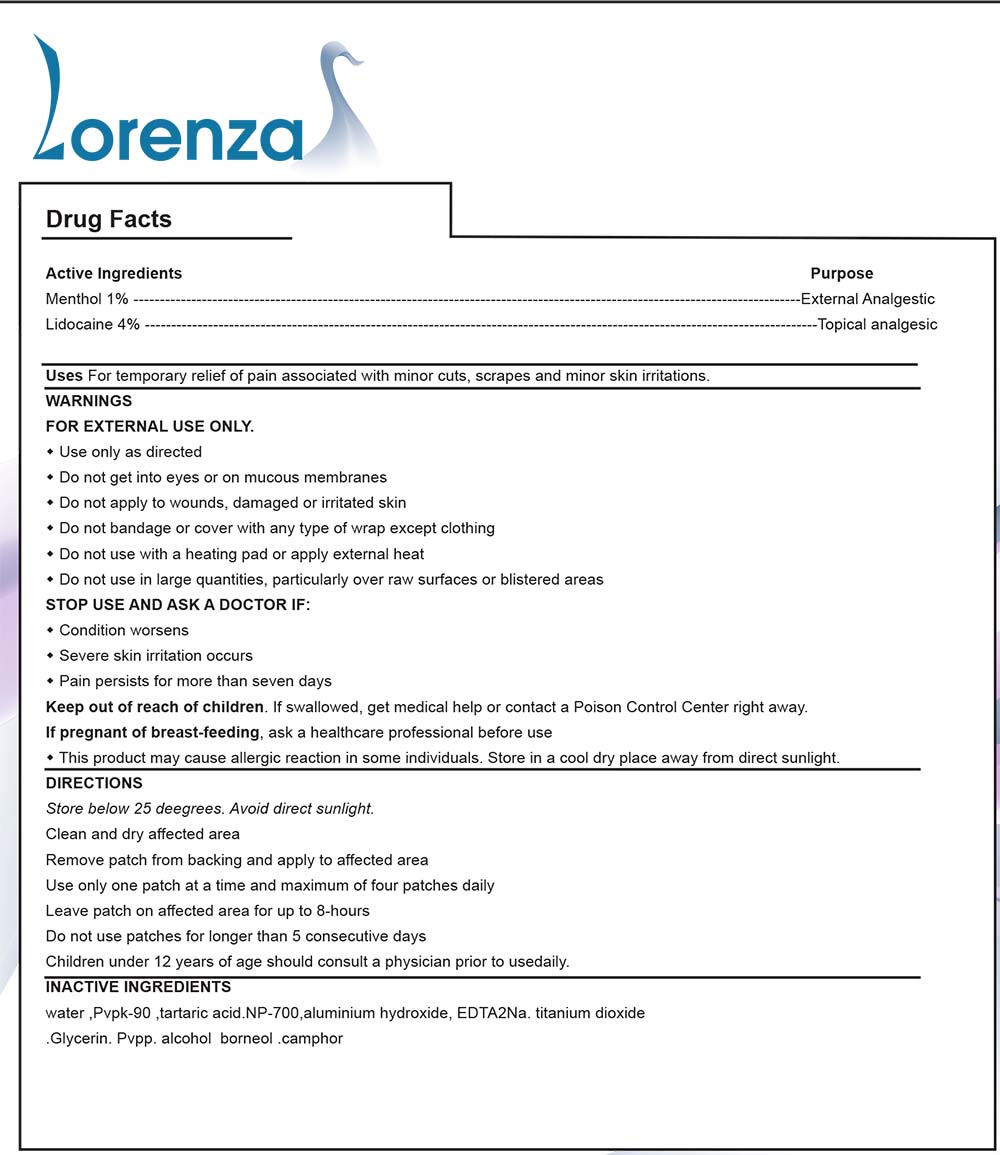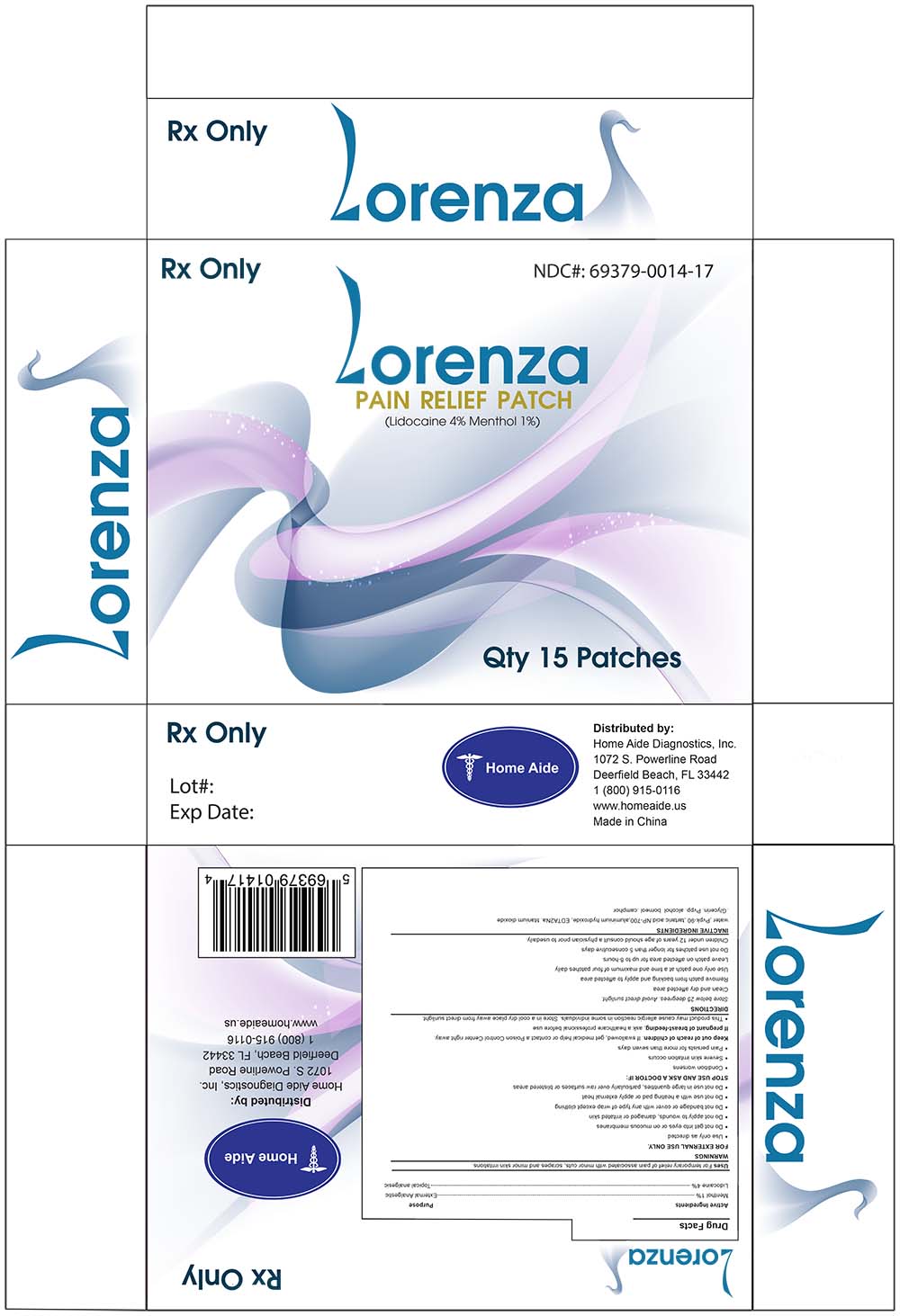 DRUG LABEL: Lorenza Pain Relief Patch
NDC: 69379-014 | Form: PATCH
Manufacturer: Home Aide Diagnostics, Inc.
Category: prescription | Type: HUMAN PRESCRIPTION DRUG LABEL
Date: 20141205

ACTIVE INGREDIENTS: Lidocaine 4 g/100 g; Menthol 1 g/100 g

LORENZA PAIN RELIEF PATCH

GENERAL PRECAUTIONS

This product may cause allergic reactions in some individuals.